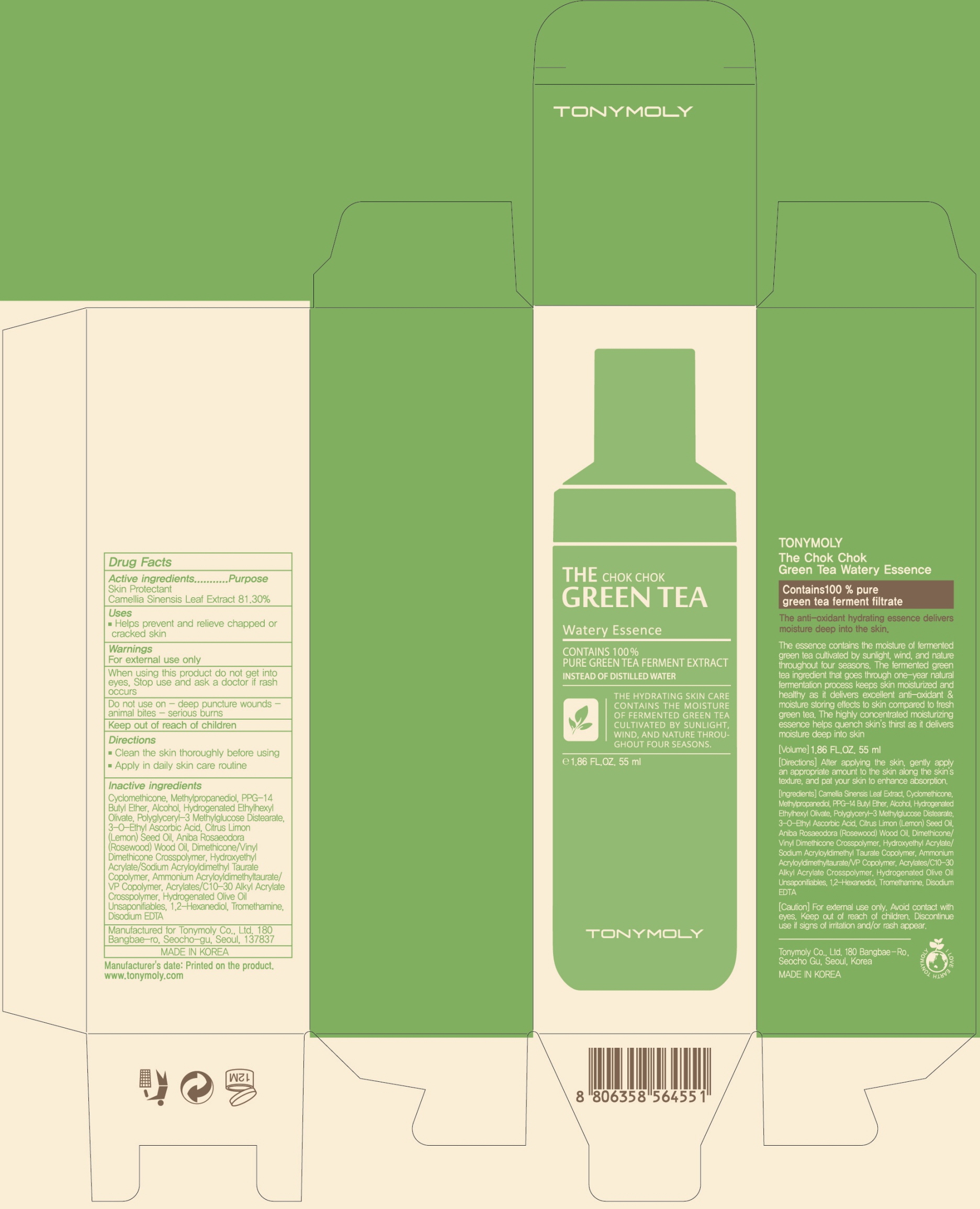 DRUG LABEL: The Chok Chok Green Tea Watery Essence
NDC: 59078-302 | Form: CREAM
Manufacturer: TONYMOLY CO.,LTD
Category: otc | Type: HUMAN OTC DRUG LABEL
Date: 20160601

ACTIVE INGREDIENTS: GREEN TEA LEAF 44.71 g/55 mL
INACTIVE INGREDIENTS: Cyclomethicone; Methylpropanediol

ACTIVE INGREDIENT

Active ingredient: Camellia Sinensis Leaf Extract 81.30%

INACTIVE INGREDIENT

Inactive Ingredient: Cyclomethicone, Methylpropanediol, PPG-14 Butyl Ether, Alcohol, Hydrogenated Ethylhexyl Olivate, Polyglyceryl-3 Methylglucose Distearate, 3-O-Ethyl Ascorbic Acid, Citrus Limon (Lemon) Seed Oil, Aniba Rosaeodora (Rosewood) Wood Oil, Dimethicone/Vinyl Dimethicone Crosspolymer, Hydroxyethyl Acrylate/Sodium Acryloyldimethyl Taurate Copolymer, Ammonium Acryloyldimethyltaurate/VP Copolymer, Acrylates/C10-30 Alkyl Acrylate Crosspolymer, Hydrogenated Olive Oil Unsaponifiables, 1,2-Hexanediol, Tromethamine, Disodium EDTA

PURPOSE

Purpose: Skin Protectant

WARNINGS

Warnings: For external use only. When using this product do not get into eyes. Stop use and ask a doctor if rash occurs. Do not use on - deep puncture wounds - animal bites - serious burns Keep out of reach of children.

KEEP OUT OF REACH OF CHILDREN

Use

Use: helps prevent and relieve chapped or cracked skin

Directions

Directions: - Clean the skin thoroughly before using - Apply in daily skin care routine